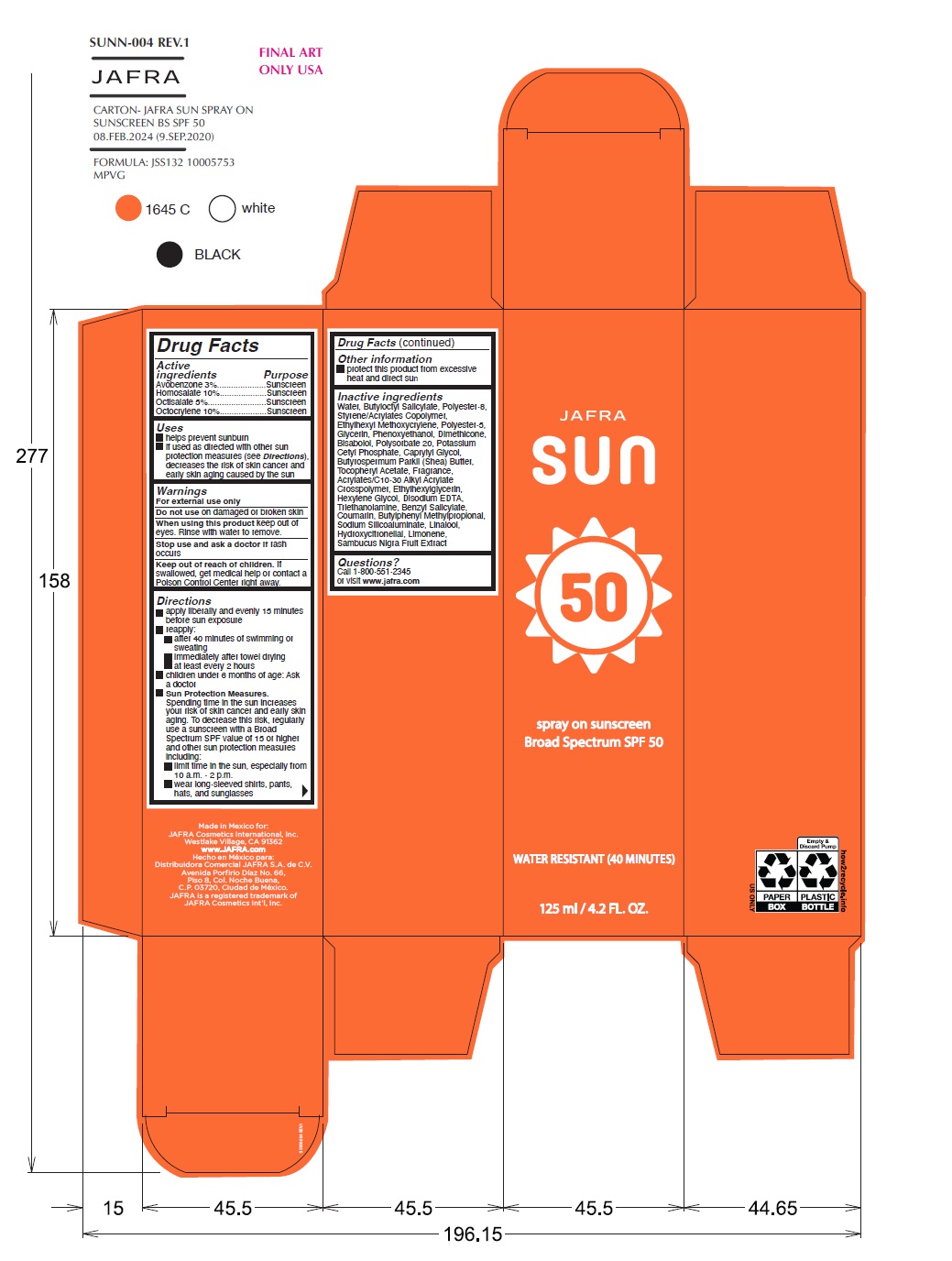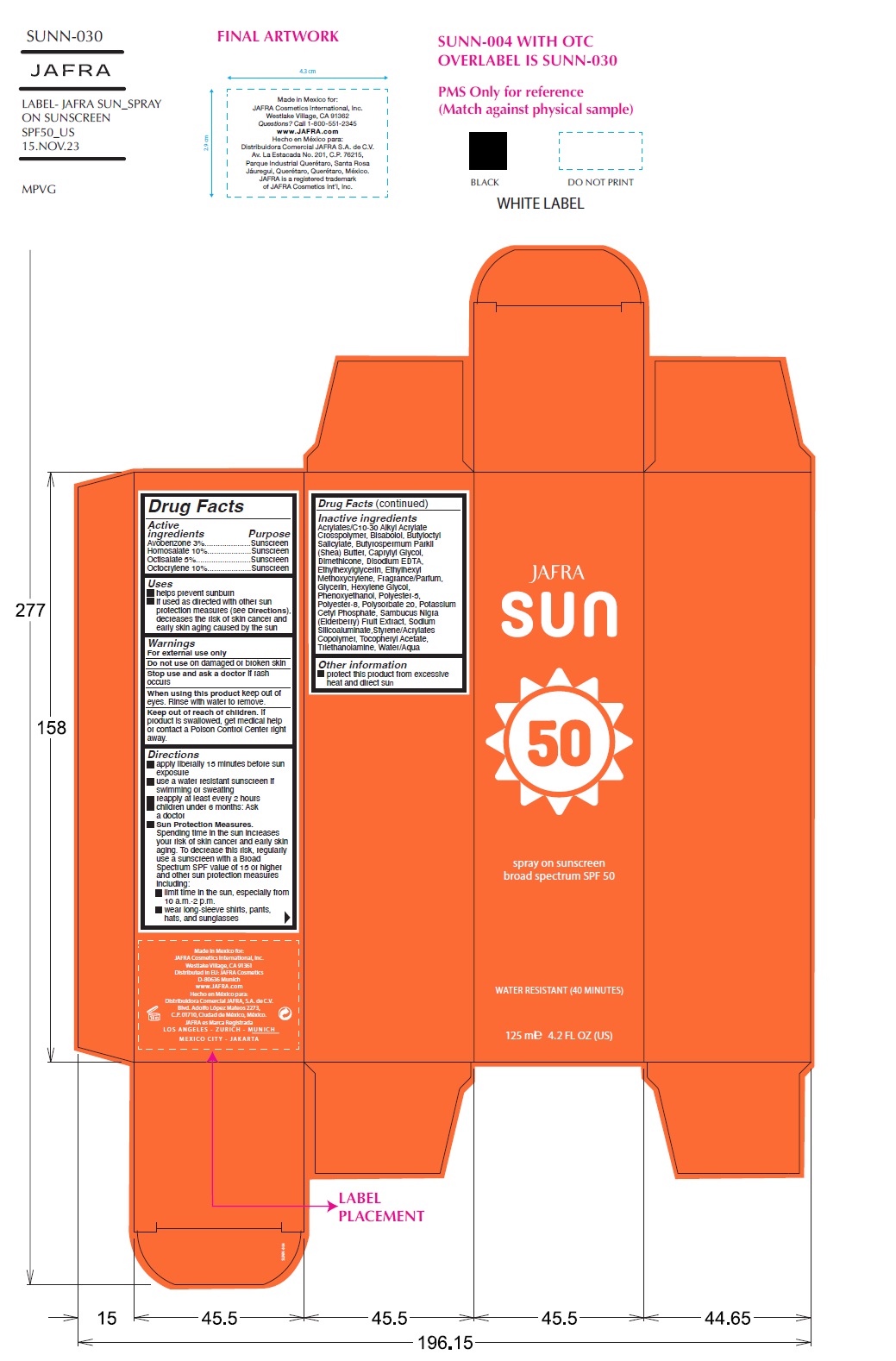 DRUG LABEL: Jafra Sun sunscreen broad spectrum SPF 50
NDC: 68828-296 | Form: SPRAY
Manufacturer: Distribuidora Comercial Jafra, S.A. de C.V.
Category: otc | Type: HUMAN OTC DRUG LABEL
Date: 20251021

ACTIVE INGREDIENTS: AVOBENZONE 3 g/100 mL; HOMOSALATE 10 g/100 mL; OCTISALATE 5 g/100 mL; OCTOCRYLENE 10 g/100 mL
INACTIVE INGREDIENTS: SODIUM ALUMINOSILICATE; HEXYLENE GLYCOL; PHENOXYETHANOL; TROLAMINE; POLYESTER-5 (TG-38); POLYESTER-8 (1400 MW, CYANODIPHENYLPROPENOYL CAPPED); POLYSORBATE 20; ETHYLHEXYL METHOXYCRYLENE; DIMETHICONE; POTASSIUM CETYL PHOSPHATE; .ALPHA.-TOCOPHEROL ACETATE; WATER; CARBOMER COPOLYMER TYPE B (ALLYL PENTAERYTHRITOL CROSSLINKED); LEVOMENOL; CAPRYLYL GLYCOL; EDETATE DISODIUM; GLYCERIN; ETHYLHEXYLGLYCERIN; EUROPEAN ELDERBERRY; BUTYLOCTYL SALICYLATE; SHEA BUTTER; BENZYL SALICYLATE; COUMARIN; BUTYLPHENYL METHYLPROPIONAL; HYDROXYCITRONELLAL; LIMONENE, (+)-; LINALOOL, (+/-)-

Jafra Sun spray on sunscreen broad spectrum SPF 50

Active Ingredients Purpose

Avobenzone 3% Sunscreen

Homosalate 10% Sunscreen

Octisalate 5% Sunscreen

Octocrylene 10% Sunscreen

Uses

- Helps Prevent Sunburn
- If used as directed with other sun protection measures (see Directions), decreases the risk of skin cancer and early skin aging caused by the sun.

Warnings

- For external use only
- Do not useon damaged or broken skin
- When using this productkeep out of eyes. Rinse with water to remove.
- Stop use and ask a doctor if rash occurs
- Keep out of reach of children.If swallowed, get medical help or contact a poison Control Center right away

Directions

- Apply liberally and evenly 15 minutes before sun exposure
- reapply:

• after 40 minutes of swimming or sweating
• immediately after towel drying
• at least every 2 hours

- Children under 6 months of age: ask a doctor.
- Sun Protection Measures: Spending time in the sun increases your risk of skin cancer and early skin aging. To decrease this risk, regularly use a sunscreen with a Broad-Spectrum SPF value of 15 or higher and other sun protection measures including:

• limit your time in the sun, especially from 10a.m. – 2 p.m.

• wear long-sleeved shirts, pants, hats, and sunglasses

Other information

- protect this product from excessive heat and direct sun

Inactive Ingredients

Water, Butyloctyl Salicylate, Polyester-8, Styrene/Acrylates Copolymer, Ethylhexyl Methoxycrylene, Polyester-5, Glycerin, Phenoxyethanol, Dimethicone, Bisabolol, Polysorbate 20, Potassium Cetyl Phosphate, Caprylyl Glycol, Butyrospermum Parkii (Shea) Butter, Tocopheryl Acetate, Fragrance, Acrylates/C10-30 Alkyl Acrylate Crosspolymer, Ethylhexylglycerin, Hexylene Glycol, Disodium EDTA, Triethanolamine, Benzyl Salicylate , Coumarin, Butylphenyl Methylpropional, Sodium Silicoaluminate, Linalool, Hydroxycitronellal, Limonene, Sambucus Nigra Fruit Extract

Questions?Call 1-800-551-2345 or visit www.jafra.com